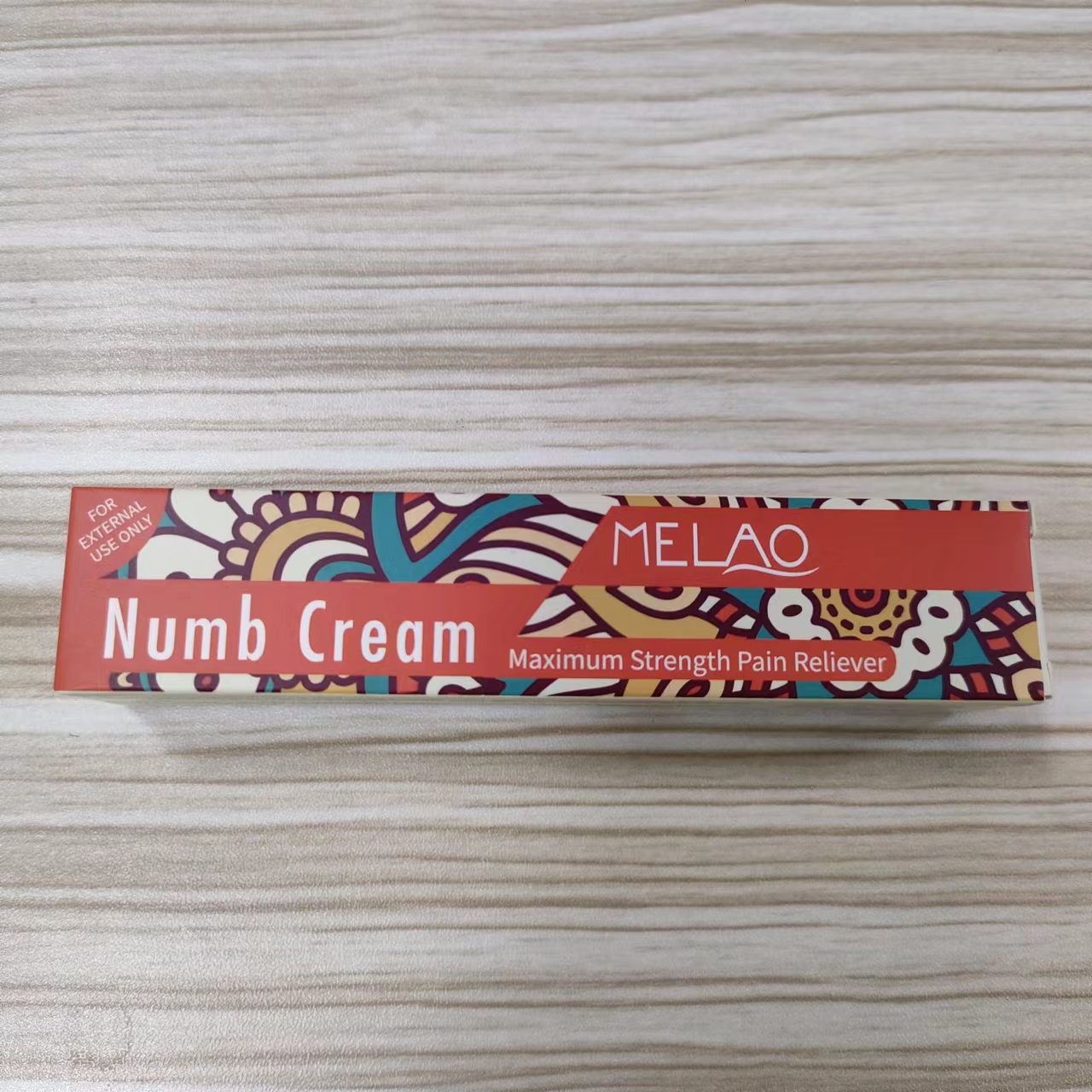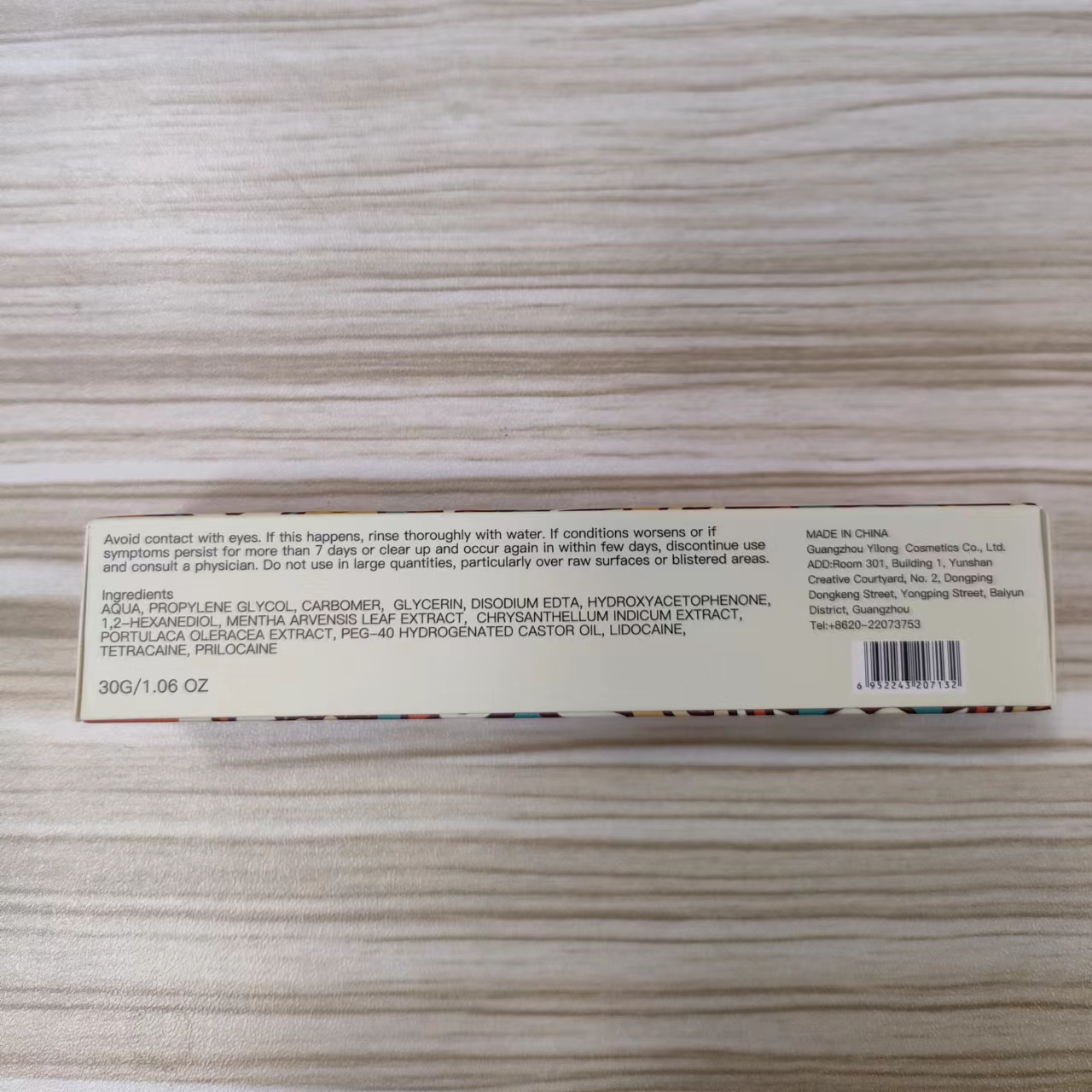 DRUG LABEL: MELAO Numb Cream
NDC: 83566-257 | Form: OIL
Manufacturer: Guangzhou Yilong Cosmetics Co., Ltd
Category: otc | Type: HUMAN OTC DRUG LABEL
Date: 20240712

ACTIVE INGREDIENTS: LIDOCAINE N2-OXIDE 20 g/100 g
INACTIVE INGREDIENTS: MENTHA ARVENSIS LEAF; PORTULACA OLERACEA LEAF; PROPYLENE GLYCOL 1-(2-METHYLBUTYRATE); 1,2-HEXANEDIOL; WATER; HYDROXYACETOPHENONE; TETRACAINE; GLYCERIN; DISODIUM EDTA-COPPER; CHRYSANTHELLUM INDICUM FLOWER; PRILOCAINE; HYDROGENATED CASTOR OIL; CARBOMER 980

MELAO Numb Cream

INACTIVE INGREDIENT

Aqua. PROPYLENE GLYCOL, CARBOMER, GLYCERIN, DISODIUM EDTA, HYDROXYACETOPHENONE.1.2-HEXANEDIOL MENTHA ARVENSIS LEAF EXTRACT, CHRYSANTHELLUM INDICUM EXTRACT.PORTULACA OLERACEA EXTRACT, PEG-40 HYDROGENATED CASTOR OIL,TETRACAINE,PRILOCAINE

ACTIVE INGREDIENT

LIDOCAINE

PURPOSE

For temporary relief of local discomfort, itching,pain,soreness or burning in the perianal area associated with anorectal disorders.

INDICATIONS AND USAGE

1.Adults: When practical, cleanse the affected area with mild soap, and warm water and rinse thoroughly. Gently dry by patting or blotting with tissue or a soft cloth before application of the product.

2. Apply externally to the affected area up to 6 timesdaily.

3. Children under 12 years of age: consult a doctor.

WARNINGS

For external use only.

Seal the product and avoidlight, store in a cool and dnpiace.

Stop use and ask a doctor if allergic reaction occurs rectal bleeding occurs redness, iritation, swelling,pain or other symptoms begin or increase condition worsens or does not improve within 7 days

DO NOT USE

Do not exceed the recommended daily dosage unless directed by a doctor.

Do not put into the rectum by using fngers or any mechanical device or applicator.

When using this product keep out of eyes. Rinse with water to remove.

Keep out of reach of children. If swallowed, get medical help or contact a Poison Control Center right away.

DOSAGE AND ADMINISTRATION

1.Adults: When practical, cleanse the affected area with mild soap, and warm water and rinse thoroughly. Gently dry by patting or blotting with tissue or a soft cloth before application of the product.

2. Apply externally to the affected area up to 6 timesdaily.

3. Children under 12 years of age: consult a doctor.